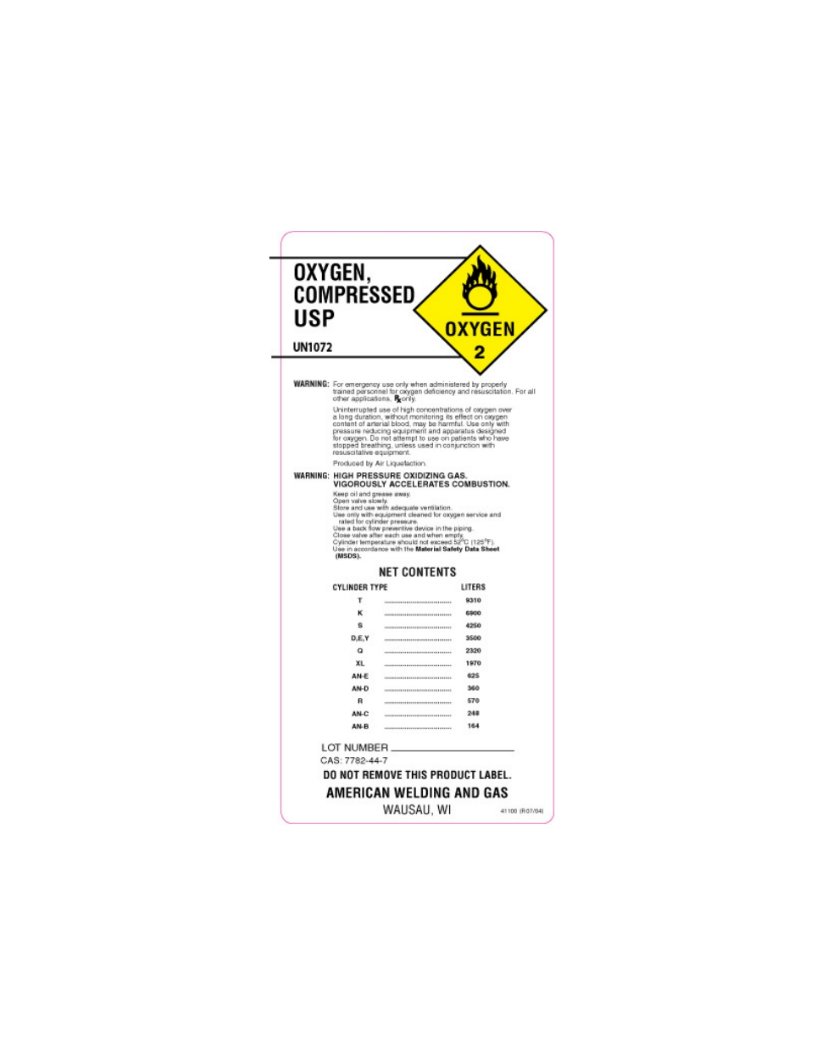 DRUG LABEL: Oxygen
NDC: 10825-001 | Form: GAS
Manufacturer: Northern Welding Supply
Category: prescription | Type: HUMAN PRESCRIPTION DRUG LABEL
Date: 20101001

ACTIVE INGREDIENTS: Oxygen 99 L/100 L

Compressed Oxygen Label

PACKAGE LABEL

OXYGEN, COMPRESSED USP

UN1072

WARNING: For emergency use only when administered by properly trained personnel for oxygen deficiency and resuscitation. For all other applications, Rx only.

Uninterrupted use of high concentrations of oxygen over a long duration, without monitoring its effect on oxygen content of arterial blood, may be harmful. Use only with pressure reducing equpment and apparatus designed for oxygen. Do not attempt to use on patients who have stopped breathing. Unless used in conjunction with resuscitative equipment.

Produced by Air Liquefaction.

WARNING: HIGH PRESSURE OXIDIZING GAS.

VIGOROUSLY ACCELERATES COMBUSTION.

Keep oil and grease away.

Open valve slowly.

Store and use with adequate ventilation.

Use only with equipment cleaned for oxygen service and rated for cylinder pressure.

Use a back flow preventive device in the piping.

Close valve after each use and when empty.

Cylinder temperature should not exceed 52C (125F).

Use in accordance with the

Material Safety Data Sheet (MSDS).

NET CONTENTS
CYLINDER TYPE LITERS
T 9310
K 6900
S 4250
D, E, Y 3500
Q 2320
XL 1970
AN-E 625
AN-D 360
R 570
AN-C 248
AN-B 164
LOT NUMBER____________________
DO NOT REMOVE THIS PRODUCT LABEL
AMERICAN WELDING AND GAS
WAUSAU, WI